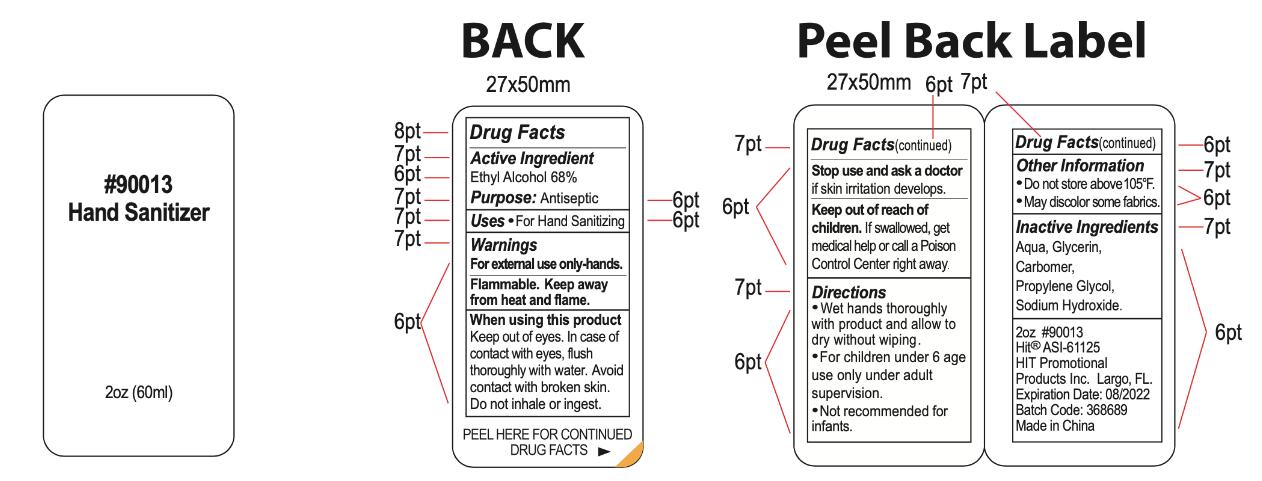 DRUG LABEL: 90013 Hand Sanitizer
NDC: 74274-200 | Form: GEL
Manufacturer: Huizhou Bliss Commodity Co., Ltd
Category: otc | Type: HUMAN OTC DRUG LABEL
Date: 20200902

ACTIVE INGREDIENTS: ALCOHOL 68 g/112 mL
INACTIVE INGREDIENTS: SODIUM HYDROXIDE; CARBOMER HOMOPOLYMER, UNSPECIFIED TYPE; WATER; GLYCERIN; PROPYLENE GLYCOL

74274-200
90013 Hand Sanitizer

ACTIVE INGREDIENT

Ethyl Alcohol(68% w/w)
68g/112mL

PURPOSE

Antiseptic

INDICATIONS AND USAGE

For Hand Sanitizing

WARNINGS

For external use only-hands.
Flammable. Keep away from heat and flame.

When using this product Keep out of eyes. In case of contact with eyes, flush thoroughly with water. Avoid contact with broken skin. Do not inhale or ingest.

Stop use and ask a doctor if skin irritation develops.

Keep out of reach of children. If swallo'Ned, get medical help or call a Poison Control Center right away.

DO NOT USE

/

When using this product Keep out of eyes. In case of contact with eyes, flush thoroughly with water. Avoid contact with broken skin. Do not inhale or ingest.

Stop use and ask a doctor if skin irritation develops.

Keep out of reach of children. If swallo'Ned, get medical help or call a Poison Control Center right away.

DOSAGE AND ADMINISTRATION

Wet hands thoroughly with product and allow to dry without wiping.
For children under 6 ageuse only under adult supervision.
Not recommended for infants.

STORAGE AND HANDLING

Do not store above 105F.
May discolor some fabrics.

INACTIVE INGREDIENT

Aqua, Glycerin, Carbomer, Propylene Glycol, Sodium Hydroxide